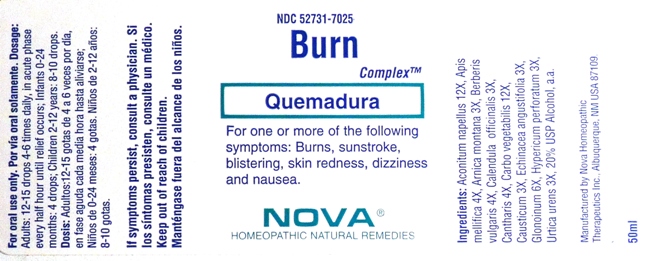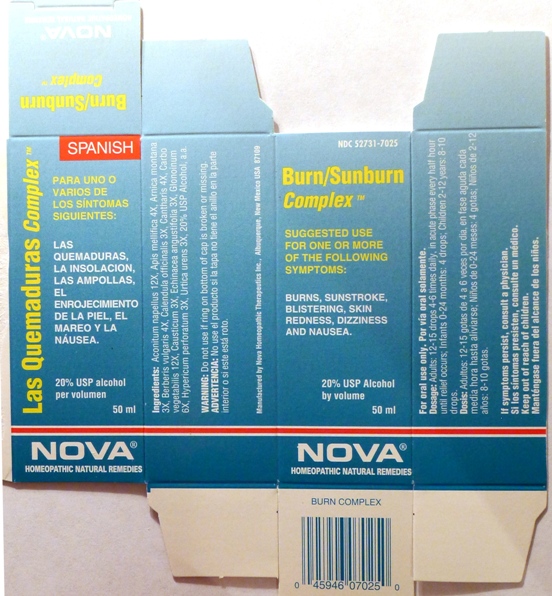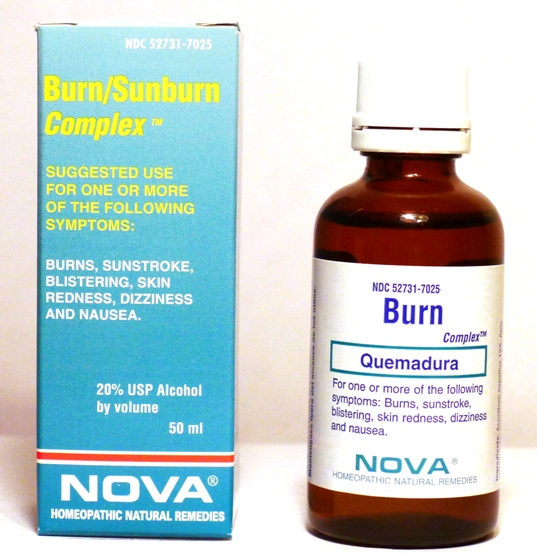 DRUG LABEL: Burn Complex
NDC: 52731-7025 | Form: LIQUID
Manufacturer: Nova Homeopathic Therapeutics, Inc.
Category: homeopathic | Type: HUMAN OTC DRUG LABEL
Date: 20110601

ACTIVE INGREDIENTS: ACONITUM NAPELLUS 12 [hp_X]/1 mL; APIS MELLIFERA 4 [hp_X]/1 mL; ARNICA MONTANA 3 [hp_X]/1 mL; BERBERIS VULGARIS ROOT BARK 4 [hp_X]/1 mL; CALENDULA OFFICINALIS FLOWERING TOP 3 [hp_X]/1 mL; LYTTA VESICATORIA 4 [hp_X]/1 mL; ACTIVATED CHARCOAL 12 [hp_X]/1 mL; CAUSTICUM 3 [hp_X]/1 mL; ECHINACEA ANGUSTIFOLIA 3 [hp_X]/1 mL; NITROGLYCERIN 6 [hp_X]/1 mL; HYPERICUM PERFORATUM 3 [hp_X]/1 mL; URTICA URENS 3 [hp_X]/1 mL
INACTIVE INGREDIENTS: ALCOHOL 10 mL/50 mL

Burn Complex

Purpose:

Suggested use for one or more of the following symptoms:
Burns, sunstroke, blistering, skin redness, dizziness and nausea.

Usage and Dosage:

For oral use only.

DOSAGE AND ADMINISTRATION

Adults:
In Acute Phase:
12-15 drops, every half hour until relief occurs
When Relief Occurs:
12-15 drops, 4-6 times per day
Children 2-12 years:
8-10 drops, 4-6 times per day
Infants 0-24 months:
4 drops, 4-6 times per day

Warnings:

Keep out of reach of children.

WARNINGS

If symptoms persist, consult a physician.

Do not use if ring on bottom of cap is broken or missing.

Active Ingredients:

Aconitum napellus 12X, Apis mellifica 4X, Arnica montana 3X, Berberis vulgaris 4X, Calendula officinalis 3X, Cantharis 4X, Carbo vegetabilis 12X, Causticum 3X, Echinacea angustifolia 3X, Glonoinum 6X, Hypericum perforatum 3X, Urtica urens 3X

Inactive Ingredients:

Alcohol, 20% USP

QUESTIONS

Manufactured by Nova Homeopathic Therapeutics Inc., Albuquerque, New Mexico USA 87109
1-800-225-8094

PACKAGE LABEL

Burn Complex Product

Burn Complex Bottle Label

Burn Complex Box